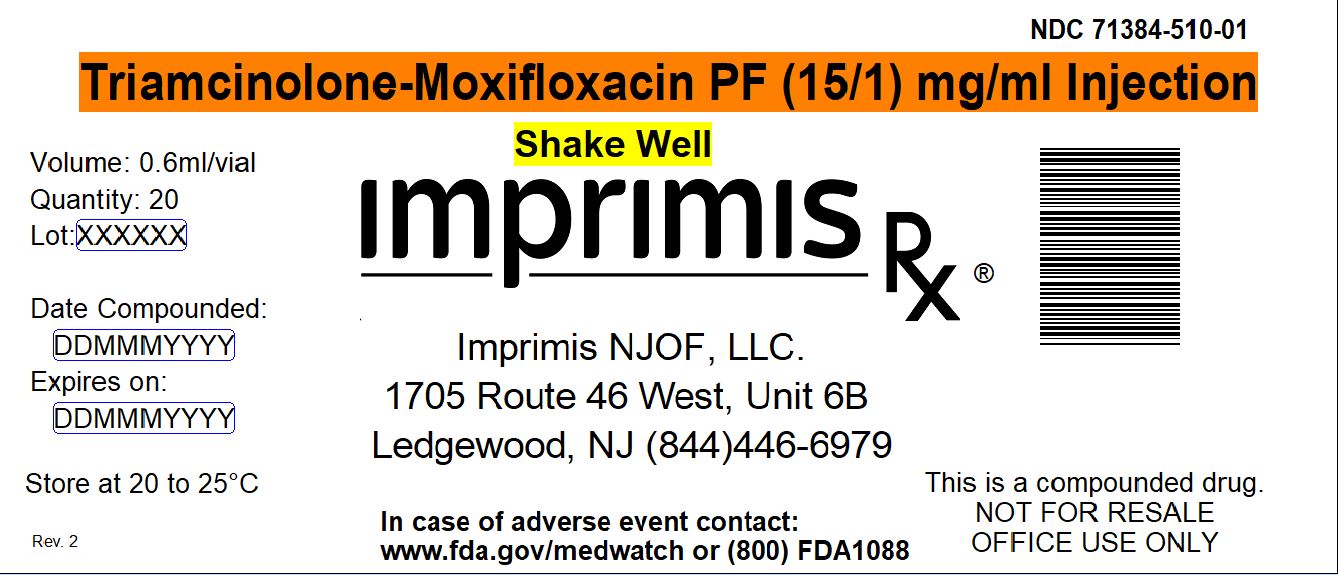 DRUG LABEL: Triamcinolone-Moxifloxacin PF
NDC: 71384-510 | Form: INJECTION, SUSPENSION
Manufacturer: Imprimis NJOF, LLC
Category: prescription | Type: HUMAN PRESCRIPTION DRUG LABEL
Date: 20200210

ACTIVE INGREDIENTS: TRIAMCINOLONE ACETONIDE 15 mg/1 mL; MOXIFLOXACIN HYDROCHLORIDE MONOHYDRATE 1 mg/1 mL

STORAGE AND HANDLING

Store at 20° to 25° C (68° to 77° F)